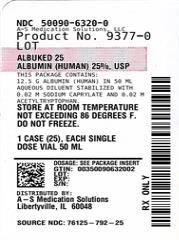 DRUG LABEL: ALBUKED
NDC: 50090-6320 | Form: SOLUTION
Manufacturer: A-S Medication Solutions
Category: other | Type: PLASMA DERIVATIVE
Date: 20240628

ACTIVE INGREDIENTS: ALBUMIN HUMAN 5 g/20 mL
INACTIVE INGREDIENTS: Acetyltryptophan, Dl-; Sodium Caprylate; Water

ALBUKED

DESCRIPTION

Albumin (Human) 25%, USP (Albuked™ 25) is made from large pools of human venous plasma by the Cohn cold ethanol fractionation process. Part of the fractionation may be performed by another licensed manufacturer. It is prepared in accordance with the applicable requirements established by the U.S. Food and Drug Administration.

Albuked 25 is a 25% sterile solution of albumin in an aqueous diluent. The preparation is stabilized with 0.02 M sodium caprylate and 0.02 M acetyltryptophan. The aluminum content of the product is not more than 200 µg/L. The approximate sodium content of the product is 145 mEq/L. Albuked 25 is clear, slightly viscous, almost colorless to yellow, amber or green. It contains no preservative. Albuked 25 must be administered intravenously.

Each vial of Albuked 25 is heat-treated at 60°C for 10 hours against the possibility of transmitting the hepatitis viruses.

Additionally, the manufacturing process was investigated for its capacity to decrease the infectivity of an experimental agent of transmissible spongiform encephalopathy (TSE), considered as a model for the variant Creutzfeldt-Jakob disease (vCJD) and Creutzfeldt-Jakob disease (CJD) agents.(11-14) The production steps from Pooled Plasma to Effluent IV-1 in the Albuked 25 manufacturing process have been shown to decrease TSE infectivity of that experimental model agent (a total of ≥7.0 logs). These studies provide reasonable assurance that low levels of vCJD/CJD agent infectivity, if present in the starting material, would be removed.

CLINICAL PHARMACOLOGY

Each 20 mL vial of Albuked 25 supplies the oncotic equivalent of approximately 100 mL citrated plasma; 50 mL supplies the oncotic equivalent of approximately 250 mL citrated plasma.

When administered intravenously to an adequately hydrated subject, the oncotic (colloid osmotic) effect of 20 mL Albuked 25 is such that it will draw approximately a further 70 mL of fluid from the extravascular tissues into the circulation within 15 minutes,(1) thus increasing the total blood volume and reducing both hemoconcentration and whole blood viscosity. Accordingly, the main clinical indications are for hypoproteinemic states involving reduced oncotic pressure, with or without accompanying edema.(2) Albuked 25 can also be used as a plasma volume expander.

Albumin is a transport protein and it may be useful in severe hemolytic disease in the neonate who is awaiting exchange transfusion. The infused albumin may reduce the level of free bilirubin in the blood.(2,3) This could also be of importance in acute liver failure where albumin might serve the dual role of supporting plasma oncotic pressure, as well as binding excessive plasma bilirubin.(2)

INDICATIONS AND USAGE

Emergency Treatment of Hypovolemic Shock

Albuked 25 is hyperoncotic and on intravenous infusion will expand the plasma volume by an additional amount, three to four times the volume actually administered, by withdrawing fluid from the interstitial spaces, provided the patient is normally hydrated interstitially or there is interstitial edema.(1) If the patient is dehydrated, additional crystalloids must be given,(4) or alternatively, Albumin (Human) 5%, USP (Albuked™ 5) should be used. The patient’s hemodynamic response should be monitored and the usual precautions against circulatory overload observed. The total dose should not exceed the level of albumin found in the normal individual, i.e., about 2 g per kg body weight in the absence of active bleeding. Although Albuked 5 is to be preferred for the usual volume deficits, Albuked 25 with appropriate crystalloids may offer therapeutic advantages in oncotic deficits or in long-standing shock where treatment has been delayed.(2)

Removal of ascitic fluid from a patient with cirrhosis may cause changes in cardiovascular function and even result in hypovolemic shock. In such circumstances, the use of an albumin infusion may be required to support the blood volume.(2)

Burn Therapy

An optimal therapeutic regimen with respect to the administration of colloids, crystalloids, and water following extensive burns has not been established. During the first 24 hours after sustaining thermal injury, large volumes of crystalloids are infused to restore the depleted extracellular fluid volume. Beyond 24 hours Albuked 25 can be used to maintain plasma colloid osmotic pressure.

Hypoproteinemia With or Without Edema

During major surgery, patients can lose over half of their circulating albumin with the attendant complications of oncotic deficit.(2,4,5) A similar situation can occur in sepsis or intensive care patients. Treatment with Albuked 25 may be of value in such cases.(2)

Adult Respiratory Distress Syndrome (ARDS)(2,5)

This is characterized by deficient oxygenation caused by pulmonary interstitial edema complicating shock and postsurgical conditions. When clinical signs are those of hypoproteinemia with a fluid volume overload, Albuked 25 together with a diuretic may play a role in therapy.

Cardiopulmonary Bypass(2,6)

With the relatively small priming volume required with modern pumps, preoperative dilution of the blood using albumin and crystalloid has been shown to be safe and well-tolerated. Although the limit to which the hematocrit and plasma protein concentration can be safely lowered has not been defined, it is common practice to adjust the albumin and crystalloid pump prime to achieve a hematocrit of 20% and a plasma albumin concentration of 2.5 g per 100 mL in the patient.

Acute Liver Failure (2)

In the uncommon situation of rapid loss of liver function with or without coma, administration of albumin may serve the double purpose of supporting the colloid osmotic pressure of the plasma as well as binding excess plasma bilirubin.

Neonatal Hemolytic Disease(2,3)

The administration of Albuked 25 may be indicated prior to exchange transfusion, in order to bind free bilirubin, thus lessening the risk of kernicterus. A dosage of 1 g /kg body weight is given about 1 hour prior to exchange transfusion. Caution must be observed in hypervolemic infants.

Sequestration of Protein Rich Fluids(7)

This occurs in such conditions as acute peritonitis, pancreatitis, mediastinitis, and extensive cellulitis. The magnitude of loss into the third space may require treatment of reduced volume or oncotic activity with an infusion of albumin.

Erythrocyte Resuspension(2)

Albumin may be required to avoid excessive hypoproteinemia, during certain types of exchange transfusion, or with the use of very large volumes of previously frozen or washed red cells. About 25 g of albumin per liter of erythrocytes is commonly used, although the requirements in preexistent hypoproteinemia or hepatic impairment can be greater. Albuked 25 is added to the isotonic suspension of washed red cells immediately prior to transfusion.

Acute Nephrosis(2)

Certain patients may not respond to cyclophosphamide or steroid therapy. The steroids may even aggravate the underlying edema. In this situation a loop diuretic and 100 mL Albuked 25 repeated daily for 7 to 10 days may be helpful in controlling the edema and the patient may then respond to steroid treatment.

Renal Dialysis(2)

Although not part of the regular regimen of renal dialysis, Albuked 25 may be of value in the treatment of shock or hypotension in these patients. The usual volume administered is about 100 mL, taking particular care to avoid fluid overload as these patients are often fluid overloaded and cannot tolerate substantial volumes of salt solution.

Situations in Which Albumin Administration is Not Warranted(2)

In chronic nephrosis, infused albumin is promptly excreted by the kidneys with no relief of the chronic edema or effect on the underlying renal lesion. It is of occasional use in the rapid “priming” diuresis of nephrosis. Similarly, in hypoproteinemic states associated with chronic cirrhosis, malabsorption, protein losing enteropathies, pancreatic insufficiency, and undernutrition, the infusion of albumin as a source of protein nutrition is not justified.

CONTRAINDICATIONS

Certain patients, e.g., those with a history of congestive cardiac failure, renal insufficiency or stabilized chronic anemia, are at special risk of developing circulatory overload. A history of an allergic reaction to albumin is a specific contraindication to usage.

WARNINGS

Albumin (Human) 25%, USP (Albuked™ 25) is made from human plasma. Products made from human plasma may contain infectious agents, such as viruses, and, theoretically, the Creutzfeldt-Jakob Disease (CJD) agent that can cause disease. The theoretical risk for transmission of CJD is considered extremely remote. No cases of transmission of viral diseases or CJD have ever been identified for albumin. The risk that such products will transmit an infectious agent has been reduced by screening plasma donors for prior exposure to certain viruses, by testing for the presence of certain current virus infections, and by inactivating and/or removing certain viruses. Despite these measures, such products can still potentially transmit disease. There is also the possibility that unknown infectious agents may be present in such products. Individuals who receive infusions of blood or plasma products may develop signs and/or symptoms of some viral infections, particularly hepatitis C. ALL infections thought by a physician possibly to have been transmitted by this product should be reported by the physician or other healthcare provider to Grifols Therapeutics LLC [1-800-520-2807].

The physician should discuss the risks and benefits of this product with the patient, before prescribing or administering it to the patient.

As with any hyperoncotic protein solution likely to be administered in large volumes, severe hemolysis and acute renal failure may result from the inappropriate use of Sterile Water for Injection as a diluent for Albumin (Human), 25%. Acceptable diluents include 0.9% Sodium Chloride or 5% Dextrose in Water. Please refer to the DOSAGE AND ADMINISTRATION section for recommended diluents.

Solutions which have been frozen should not be used. Do not use if turbid. Do not begin administration more than 4 hours after the container has been entered. Partially used vials must be discarded. Vials which are cracked or which have been previously entered or damaged should not be used, as this may have allowed the entry of microorganisms. Albuked 25 contains no preservative.

PRECAUTIONS

General

Patients should always be monitored carefully in order to guard against the possibility of circulatory overload. Albuked 25 is hyperoncotic, therefore, in the presence of dehydration, albumin must be given with or followed by addition of fluids.(4)

In hemorrhage the administration of albumin should be supplemented by the transfusion of whole blood to treat the relative anemia associated with hemodilution.(8) When circulating blood volume has been reduced, hemodilution following the administration of albumin persists for many hours. In patients with a normal blood volume, hemodilution lasts for a much shorter period.(4,9,10)

The rapid rise in blood pressure which may follow the administration of a colloid with positive oncotic activity necessitates careful observation to detect and treat severed blood vessels which may not have bled at the lower blood pressure.

Drug Interactions

Albuked 25 is compatible with whole blood, packed red cells, as well as the standard carbohydrate and electrolyte solutions intended for intravenous use. It should, however, not be mixed with protein hydrolysates, amino acid solutions nor those containing alcohol.

Pregnancy

Animal reproduction studies have not been conducted with Albuked 25. It is also not known whether Albuked 25 can cause fetal harm when administered to a pregnant woman or can affect reproduction capacity. Albuked 25 should be given to a pregnant woman only if clearly needed.

Pediatric Use

Safety and effectiveness in the pediatric population have not been established.

ADVERSE REACTIONS

Adverse reactions to albumin are rare. Such reactions may be allergic in nature or due to high plasma protein levels from excessive albumin administration. Allergic manifestations include urticaria, chills, fever, and changes in respiration, pulse and blood pressure.

DOSAGE AND ADMINISTRATION

Albuked 25 should always be administered by intravenous infusion. Albuked 25 may be administered either undiluted or diluted in 0.9% Sodium Chloride or 5% Dextrose in Water. If sodium restriction is required, Albuked 25 should only be administered either undiluted or diluted in a sodium-free carbohydrate solution such as 5% Dextrose in Water.

A number of factors beyond our control could reduce the efficacy of this product or even result in an ill effect following its use. These include improper storage and handling of the product after it leaves our hands, diagnosis, dosage, method of administration, and biological differences in individual patients. Because of these factors, it is important that this product be stored properly and that the directions be followed carefully during use.

Hypovolemic Shock—For treatment of hypovolemic shock, the volume administered and the speed of infusion should be adapted to the response of the individual patient.

Burns—After a burn injury (usually beyond 24 hours) there is a close correlation between the amount of albumin infused and the resultant increase in plasma colloid osmotic pressure. The aim should be to maintain the plasma albumin concentration in the region of 2.5 ± 0.5 g per 100 mL with a plasma oncotic pressure of 20 mm Hg (equivalent to a total plasma protein concentration of 5.2 g per 100 mL).(2) This is best achieved by the intravenous administration of Albuked 25. The duration of therapy is decided by the loss of protein from the burned areas and in the urine. In addition, oral or parenteral feeding with amino acids should be initiated, as the long-term administration of albumin should not be considered as a source of nutrition.

Hypoproteinemia With or Without Edema— Unless the underlying pathology responsible for the hypoproteinemia can be corrected, the intravenous administration of Albuked 25 must be considered purely symptomatic or supportive (see section Situations in Which Albumin Administration is Not Warranted).(2) The usual daily dose of albumin for adults is 50 to 75 g and for children 25 g. Patients with severe hypoproteinemia who continue to lose albumin may require larger quantities. Since hypoproteinemic patients usually have approximately normal blood volumes, the rate of administration of Albuked 25 should not exceed 2 mL per minute, as more rapid injection may precipitate circulatory embarrassment and pulmonary edema.

Other dosage recommendations are given under the specific indications referred to above.

Preparation for Administration

Remove seal to expose stopper. Always swab stopper top immediately with a suitable antiseptic prior to entering vial.

Parenteral drug products should be inspected visually for particulate matter and discoloration prior to administration, whenever solution and container permit.

Only 16 gauge needles or dispensing pins should be used with 20 mL vial sizes and larger. Needles or dispensing pins should only be inserted within the stopper area delineated by the raised ring. The stopper should be penetrated perpendicular to the plane of the stopper within the ring.

HOW SUPPLIED

Product: 50090-6320

NDC: 50090-6320-0 50 mL in a VIAL / 25 in a CARTON

STORAGE

Store at room temperature not exceeding 30°C (86°F). Do not freeze. Do not use after expiration date.

CAUTION

Rx only

U.S. federal law prohibits dispensing without prescription.

REFERENCES

1. Heyl JT, Gibson JG II, Janeway CA. Studies on the plasma proteins. V. The effect of concentrated solutions of human and bovine serum albumin on blood volume after acute blood loss in man. J Clin Invest. 1943;22:763-73.
2. Tullis JL. Albumin. 1. Background and use. 2. Guidelines for clinical use. JAMA. 1977;237:355-60; 460-3.
3. Comley A, Wood B. Albumin administration in exchange transfusion for hyperbilirubinaemia. Arch Dis Child. 1968;43:151-4.
4. Janeway CA, Gibson ST, Woodruff LM, Heyl JT, Bailey OT, Newhouser LR. Chemical, clinical, and immunological studies on the products of human plasma fractionation. VII. Concentrated human serum albumin. J Clin Invest. 1944;23:465-90.
5. Skillman JJ, Tanenbaum BJ. Unrecognized losses of albumin, plasma, and red cells during abdominal vascular operations. Curr Top Surg Res. 1970;2:523-33.
6. Zubiate P, Kay JH, Mendez AM, Krohn BG, Hochman R, Dunne EF. Coronary artery surgery: a new technique with use of little blood, if any. J Thorac Cardiovasc Surg. 1974;68:263-7.
7. Clowes GHA Jr, Vucinic M, Weidner MG. Circulatory and metabolic alterations associated with survival or death in peritonitis: clinical analysis of 25 cases. Ann Surg. 1966;163:866-85.
8. Heyl JT, Janeway CA. The use of human albumin in military medicine. I. The theoretical and experimental basis for its use. US Navy Med Bull. 1942;40:785-91.
9. Woodruff LM, Gibson ST. The clinical evaluation of human albumin. US Navy Med Bull. 1942;40:791-6.
10. Janeway CA, Berenberg W, Hutchins G. Indications and uses of blood, blood derivatives and blood substitutes. Med Clin North Am. 1945;29:1069-94.
11. Stenland CJ, Lee DC, Brown P, Petteway SR Jr, Rubenstein R. Partitioning of human and sheep forms of the pathogenic prion protein during the purification of therapeutic proteins from human plasma. Transfusion. 2002;42:1497-500.
12. Lee DC, Stenland CJ, Miller JL, Cai K, Ford EK, Gilligan KJ, et al. A direct relationship between the partitioning of the pathogenic prion protein and transmissible spongiform encephalopathy infectivity during the purification of plasma proteins. Transfusion. 2001;41:449-55.
13. Lee DC, Stenland CJ, Hartwell RC, Ford EK, Cai K, Miller JL, et al. Monitoring plasma processing steps with a sensitive Western blot assay for the detection of the prion protein. J Virol Methods. 2000;84:77-89.
14. Cai K, Miller JL, Stenland CJ, Gilligan KJ, Hartwell RC, Terry JC, et al. Solvent-dependent precipitation of prion protein. Biochim Biophys Acta. 2002;1597:28-35.

Manufactured for:
Kedrion Biopharma, Inc.
400 Kelby Street
Fort Lee, NJ 07024
Manufactured by:
Grifols Therapeutics LLC
Research Triangle Park, NC 27709 USA
U.S. License No. 1871

3056468
(Rev. 8/2020)